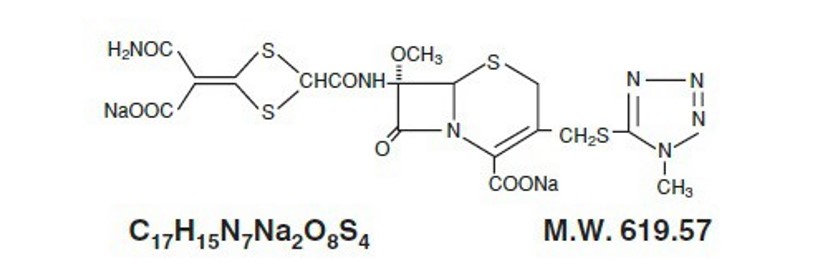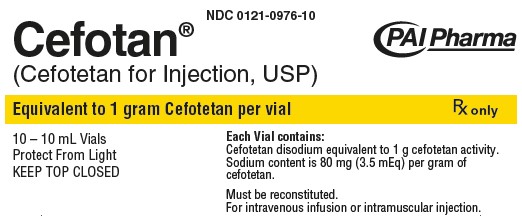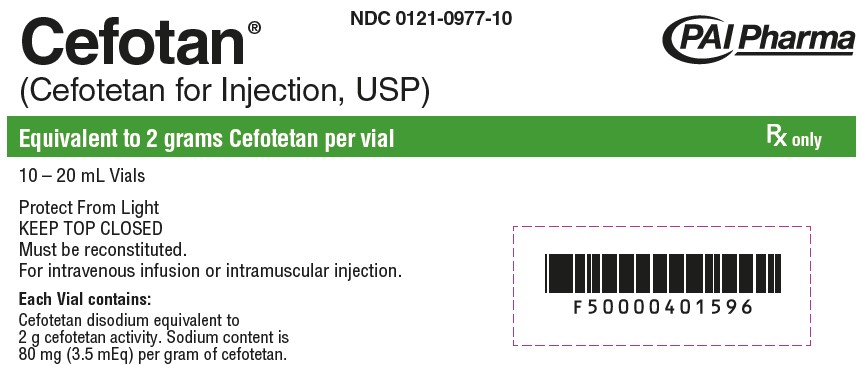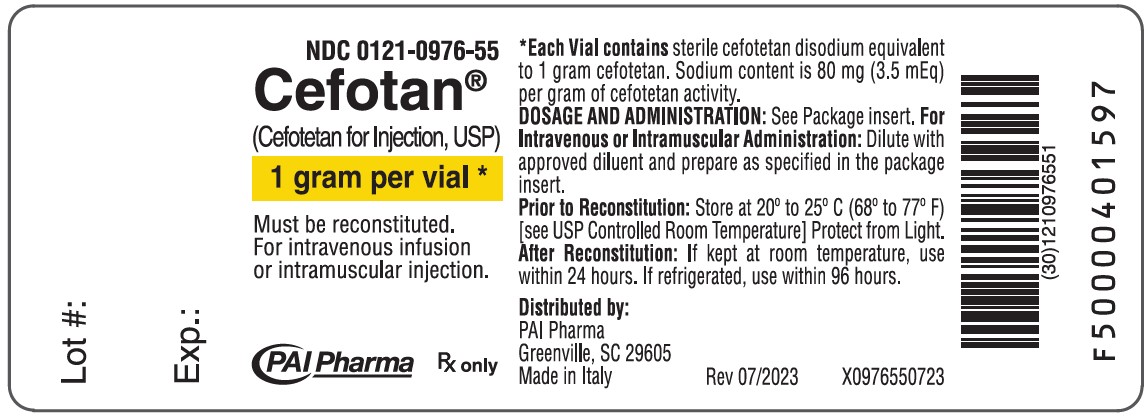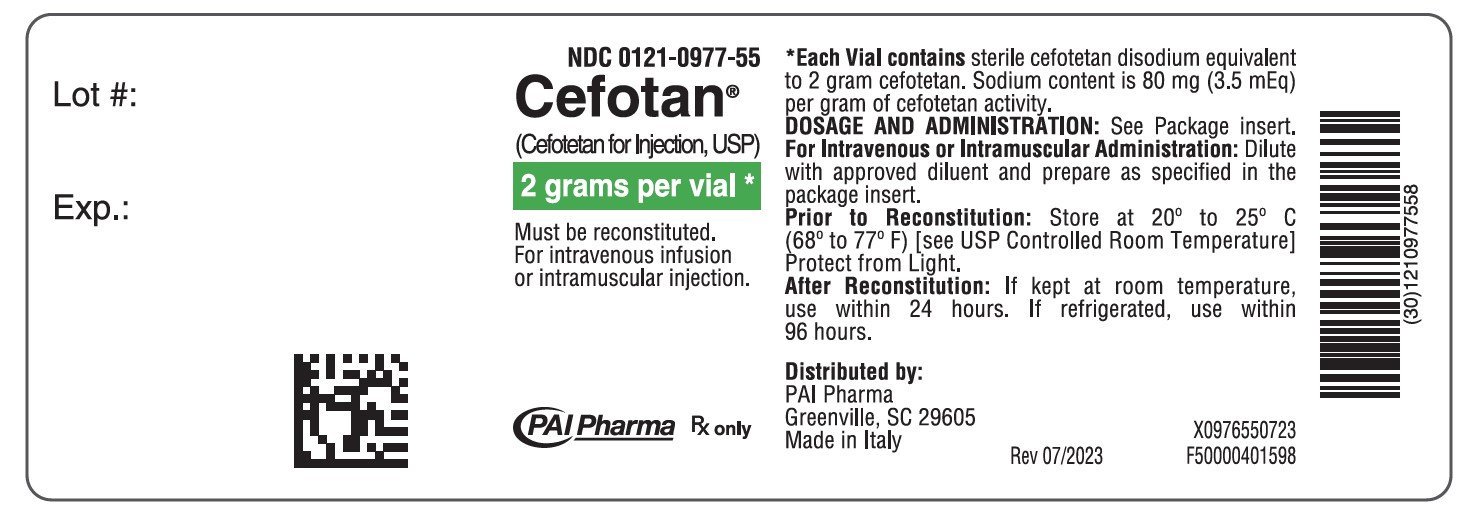 DRUG LABEL: Cefotan
NDC: 0121-0976 | Form: INJECTION, POWDER, FOR SOLUTION
Manufacturer: PAI Holdings, LLC dba PAI Pharma
Category: prescription | Type: HUMAN PRESCRIPTION DRUG LABEL
Date: 20240408

ACTIVE INGREDIENTS: CEFOTETAN DISODIUM 1 g/10 mL

CEFOTAN® (Cefotetan for Injection, USP)

Rx only

For Intravenous or Intramuscular Use

To reduce the development of drug-resistant bacteria and maintain the effectiveness of CEFOTAN® and other antibacterial drugs, CEFOTAN® should be used only to treat or prevent infections that are proven or strongly suspected to be caused by bacteria.

DESCRIPTION

CEFOTAN® (Cefotetan for Injection, USP), as cefotetan disodium, is a sterile, semisynthetic, broad-spectrum, beta-lactamase resistant, cephalosporin (cephamycin) antibiotic for parenteral administration. It is the disodium salt of [6R-(6α,7α)]-7-[[[4-(2-amino-1-carboxy-2-oxoethylidene)-1,3-dithietan-2-yl]carbonyl]amino]-7-methoxy-3-[[(1-methyl-1H-tetrazol-5-yl)thio]methyl]-8-oxo-5-thia-1-azabicyclo[4.2.0]oct-2-ene-2-carboxylic acid. Structural formula:

CEFOTAN® (Cefotetan for Injection, USP) is supplied in vials containing 80 mg (3.5 mEq) of sodium per gram of cefotetan activity. It is a white to pale yellow powder which is very soluble in water. Reconstituted solutions of CEFOTAN® (cefotetan for Injection, USP) are intended for intravenous and intramuscular administration. The solution varies from colorless to yellow depending on the concentration. The pH of freshly reconstituted solutions is usually between 4.5 to 6.5.

CEFOTAN® (Cefotetan for Injection, USP) is available in two vial strengths. Each 1 gram vial contains cefotetan disodium equivalent to 1 gram cefotetan activity. Each 2 gram vial contains cefotetan disodium equivalent to 2 grams cefotetan activity.

CLINICAL PHARMACOLOGY

High plasma levels of cefotetan are attained after intravenous and intramuscular administration of single doses to normal volunteers.

PLASMA CONCENTRATIONS AFTER 1 GRAM IVa OR IM DOSE
Mean Plasma Concentration (mcg/mL)
Time After Injection
Route | 15 min | 30 min | 1 h | 2 h | 4 h | 8 h | 12 h
IV | 92 | 158 | 103 | 72 | 42 | 18 | 9
IM | 34 | 56 | 71 | 68 | 47 | 20 | 9
a 30-minute infusion
PLASMA CONCENTRATIONS AFTER 2 GRAM IVa OR IM DOSE
Mean Plasma Concentration (mcg/mL)
Time After Injection
Route | 5 min | 10 min | 1 h | 3 h | 5 h | 9 h | 12 h
IV | 237 | 223 | 135 | 74 | 48 | 22 | 12b
IM | — | 20 | 75 | 91 | 69 | 33 | 19
a Injected over 3 minutes
b Concentrations estimated from regression line

Repeated administration of CEFOTAN® does not result in accumulation of the drug in normal subjects.

Distribution

Cefotetan is 88% plasma protein bound.

Therapeutic concentrations of cefotetan are achieved in many body tissues and fluids including:

Therapeutic levels of cefotetan are achieved in many body tissues and fluids including:

skin | ureter
muscle | bladder
fat | maxillary sinus mucosa
myometrium | tonsil
endometrium | bile
cervix | peritoneal fluid
ovary | umbilical cord serum
kidney | amniotic fluid

Metabolism and Excretion

The plasma elimination half-life of cefotetan is 3 to 4.6 hours after either intravenous or intramuscular administration.

No active metabolites of cefotetan have been detected; however, small amounts (less than 7%) of cefotetan in plasma and urine may be converted to its tautomer, which has antimicrobial activity similar to the parent drug.

In normal patients, from 51% to 81% of an administered dose of CEFOTAN® is excreted unchanged by the kidneys over a 24-hour period, which results in high and prolonged urinary concentrations. Following intravenous doses of 1 gram and 2 grams, urinary concentrations are highest during the first hour and reach concentrations of approximately 1700 and 3500 mcg/mL, respectively.

Specific Populations

Patients with Renal Impairment

In volunteers with reduced renal function, the plasma half-life of cefotetan is prolonged. The mean terminal half-life increases with declining renal function, from approximately 4 hours in volunteers with normal renal function to about 10 hours in those with moderate renal impairment. There is a linear correlation between the systemic clearance of cefotetan and creatinine clearance. When renal function is impaired, a reduced dosing schedule based on creatinine clearance must be used (see DOSAGE AND ADMINISTRATION).

Geriatric Patients

In pharmacokinetic studies of eight elderly patients (greater than 65 years) with normal renal function and six healthy volunteers (aged 25 to 28 years), mean ± SD) Total Body Clearance (1.8 ± 0.1 vs. 1.8 ± 0.3 L/h) and mean ± SD Volume of Distribution (10.4 ± 1.2 vs. 10.3 ± 1.6 L) were similar following administration of a one gram intravenous bolus dose.

Microbiology

Mechanism of Action

Cefotetan is a bactericidal agent that acts by inhibition of bacterial cell wall synthesis. Cefotetan has activity in the presence of some beta-lactamases, both penicillinases and cephalosporinases, of gram-negative and gram-positive bacteria.

Resistance

Resistance to cefotetan is primarily through hydrolysis by some beta-lactamases, alteration of penicillin-binding proteins (PBPs) and decreased permeability.

Antimicrobial Activity

Cefotetan has been shown to be active against most isolates of the following microorganisms both in vitro and in clinical infections (see INDICATIONS AND USAGE).

Gram-Negative -Bacteria

Escherichia coli

Haemophilus influenzae

Klebsiella species (including K. pneumoniae)

Morganella morganii

Neisseria gonorrhoeae

Proteus mirabilis

Proteus vulgaris

Providencia rettgeri

Serratia marcescens

Gram-Positive Bacteria

Staphylococcus aureus (methicillin-susceptible isolates only)

Staphylococcus epidermidis (methicillin-susceptible isolates only)

Streptococcus agalactiae

Streptococcus pneumoniae

Streptococcus pyogenes

Streptococcus species

Anaerobes

Prevotella bivia

Prevotella disiens

Bacteroides fragilis

Prevotella melaninogenica

Bacteroides vulgatus

Fusobacterium species

Clostridium species

Peptococcus niger

Peptostreptococcus species

The following in vitro data are available but their clinical significance is unknown. At least 90 percent of the following bacteria exhibit an in vitro minimum inhibitory concentration (MIC) less than or equal to the susceptible breakpoint for cefotetan against isolates of similar genus or organism group. However, the efficacy of cefotetan in treating clinical infections caused by these bacteria has not been established in adequate and well-controlled clinical trials.

Gram-Negative Bacteria

Citrobacter species (including C. koseri and C. freundii)

Moraxella catarrhalis

Salmonella species

Serratia species

Shigella species

Yersinia enterocolitica

Anaerobes

Porphyromonas asaccharolytica

Prevotella oralis

Bacteroides splanchnicus

Propionibacterium species

Veillonella species

Susceptibility Testing

For specific information regarding susceptibility test interpretive criteria and associated test methods and quality control standards recognized by FDA for this drug, please see: https://www.fda.gov/STIC.

INDICATIONS AND USAGE

To reduce the development of drug-resistant bacteria and maintain the effectiveness of CEFOTAN® and other antibacterial drugs, CEFOTAN® should be used only to treat or prevent infections that are proven or strongly suspected to be caused by susceptible bacteria. When culture and susceptibility information are available, they should be considered in selecting or modifying antibacterial therapy. In the absence of such data, local epidemiology and susceptibility patterns may contribute to the empiric selection of therapy.

Treatment

CEFOTAN® (Cefotetan for Injection, USP) is indicated for the therapeutic treatment of the following infections when caused by susceptible strains of the designated organisms:

Urinary Tract Infections caused by E. coli, Klebsiella spp (including K. pneumoniae), Proteus mirabilis, Proteus vulgaris, Providencia rettgeri, and Morganella morganii.

Lower Respiratory Tract Infections caused by Streptococcus pneumoniae, Staphylococcus aureus (methicillin susceptible), Haemophilus influenzae, Klebsiella species (including K. pneumoniae), E. coli, Proteus mirabilis, and Serratia marcescens.*

Skin and Skin Structure Infections due to Staphylococcus aureus (methicillin-susceptible), Staphylococcus epidermidis (methicillin susceptible), Streptococcus pyogenes, Streptococcus species, Escherichia coli, Klebsiella pneumoniae, Peptococcus niger*, Peptostreptococcus species.

Gynecologic Infections caused by Staphylococcus aureus (methicillin susceptible), Staphylococcus epidermidis (methicillin susceptible, Streptococcus species, Streptococcus agalactiae, E. coli, Proteus mirabilis, Neisseria gonorrhoeae, Bacteroides fragilis, Prevotella melaninogenica Bacteroides vulgatus, Fusobacterium species*, and gram-positive anaerobic cocci (including Peptococcus niger and Peptostreptococcus species).

Cefotetan, like other cephalosporins, has no activity against Chlamydia trachomatis. Therefore, when cephalosporins are used in the treatment of pelvic inflammatory disease, and C. trachomatis is one of the suspected pathogens, appropriate antichlamydial coverage should be added.

Intra-abdominal Infections caused by E. coli, Klebsiella species (including K. pneumoniae), Streptococcus species, Bacteroides fragilis, Prevotella melaninogenica, Bacteroides vulgatus and Clostridium species (other than Clostridium difficile [see WARNINGS])*.

Bone and Joint Infections caused by Staphylococcus aureus (methicillin susceptible)*.

* Efficacy for this organism in this organ system was studied in fewer than ten infections in clinical studies

Specimens for bacteriological examination should be obtained in order to isolate and identify causative organisms and to determine their susceptibilities to cefotetan. Therapy may be instituted before results of susceptibility studies are known; however, once these results become available, the antibiotic treatment should be adjusted accordingly.

In cases of confirmed or suspected gram-positive or gram-negative sepsis or in patients with other serious infections in which the causative organism has not been identified, it is possible to use CEFOTAN® concomitantly with an aminoglycoside. Cefotetan combinations with aminoglycosides have been shown to be synergistic in vitro against many Enterobacteriaceae and also some other gram-negative bacteria. The dosage recommended in the labeling of both antibiotics may be given and depends on the severity of the infection and the patient's condition.

NOTE: Increases in serum creatinine have occurred when CEFOTAN® was given alone. If CEFOTAN® and an aminoglycoside are used concomitantly, renal function should be carefully monitored, because nephrotoxicity may be potentiated.

Prophylaxis

The preoperative administration of CEFOTAN® may reduce the incidence of certain postoperative infections in patients undergoing surgical procedures that are classified as clean contaminated or potentially contaminated (e.g., cesarean section, abdominal or vaginal hysterectomy, transurethral surgery, biliary tract surgery, and gastrointestinal surgery).

If there are signs and symptoms of infection, specimens for culture should be obtained for identification of the causative organism so that appropriate therapeutic measures may be initiated.

CONTRAINDICATIONS

CEFOTAN® is contraindicated in patients with a known allergy to the cephalosporin group of antibiotics and in those individuals who have experienced a cephalosporin associated hemolytic anemia.

WARNINGS

BEFORE THERAPY WITH CEFOTAN® IS INSTITUTED, CAREFUL INQUIRY SHOULD BE MADE TO DETERMINE WHETHER THE PATIENT HAS HAD PREVIOUS HYPERSENSITIVITY REACTIONS TO CEFOTETAN DISODIUM, CEPHALOSPORINS, PENICILLINS, OR OTHER DRUGS. IF THIS PRODUCT IS TO BE GIVEN TO PENICILLIN-SENSITIVE PATIENTS, CAUTION SHOULD BE EXERCISED BECAUSE CROSS-HYPERSENSITIVITY AMONG BETA-LACTAM ANTIBIOTICS HAS BEEN CLEARLY DOCUMENTED AND MAY OCCUR IN UP TO 10% OF PATIENTS WITH A HISTORY OF PENICILLIN ALLERGY. IF AN ALLERGIC REACTION TO CEFOTAN® OCCURS, DISCONTINUE THE DRUG. SERIOUS ACUTE HYPERSENSITIVITY REACTIONS MAY REQUIRE TREATMENT WITH EPINEPHRINE AND OTHER EMERGENCY MEASURES, INCLUDING OXYGEN, INTRAVENOUS FLUIDS, INTRAVENOUS ANTIHISTAMINES, CORTICOSTEROIDS, PRESSOR AMINES, AND AIRWAY MANAGEMENT, AS CLINICALLY INDICATED.

AN IMMUNE MEDIATED HEMOLYTIC ANEMIA HAS BEEN OBSERVED IN PATIENTS RECEIVING CEPHALOSPORIN CLASS ANTIBIOTICS. SEVERE CASES OF HEMOLYTIC ANEMIA, INCLUDING FATALITIES, HAVE BEEN REPORTED IN ASSOCIATION WITH THE ADMINISTRATION OF CEFOTETAN. SUCH REPORTS ARE UNCOMMON. THERE APPEARS TO BE AN INCREASED RISK OF DEVELOPING HEMOLYTIC ANEMIA ON CEFOTETAN RELATIVE TO OTHER CEPHALOSPORINS OF AT LEAST 3 FOLD. IF A PATIENT DEVELOPS ANEMIA ANYTIME WITHIN 2 TO 3 WEEKS SUBSEQUENT TO THE ADMINISTRATION OF CEFOTETAN, THE DIAGNOSIS OF A CEPHALOSPORIN ASSOCIATED ANEMIA SHOULD BE CONSIDERED AND THE DRUG STOPPED UNTIL THE ETIOLOGY IS DETERMINED WITH CERTAINTY. BLOOD TRANSFUSIONS MAY BE CONSIDERED AS NEEDED (see CONTRAINDICATIONS).

PATIENTS WHO RECEIVE COURSES OF CEFOTETAN FOR TREATMENT OR PROPHYLAXIS OF INFECTIONS SHOULD HAVE PERIODIC MONITORING FOR SIGNS AND SYMPTOMS OF HEMOLYTIC ANEMIA INCLUDING A MEASUREMENT OF HEMATOLOGICAL PARAMETERS WHERE APPROPRIATE.

Clostridium difficile associated diarrhea (CDAD) has been reported with use of nearly all antibacterial agents, including cefotetan, and may range in severity from mild diarrhea to fatal colitis. Treatment with antibacterial agents alters the normal flora of the colon leading to overgrowth of C. difficile.

C. difficile produces toxins A and B which contribute to the development of CDAD. Hypertoxin producing strains of C. difficile cause increased morbidity and mortality, as these infections can be refractory to antimicrobial therapy and may require colectomy. CDAD must be considered in all patients who present with diarrhea following antibiotic use. Careful medical history is necessary since CDAD has been reported to occur over two months after the administration of antibacterial agents.

If CDAD is suspected or confirmed, ongoing antibiotic use not directed against C. difficile may need to be discontinued. Appropriate fluid and electrolyte management, protein supplementation, antibiotic treatment of C. difficile, and surgical evaluation should be instituted as clinically indicated.

In common with many other broad-spectrum antibiotics, CEFOTAN® may be associated with a fall in prothrombin activity and, possibly, subsequent bleeding. Those at increased risk include patients with renal or hepatobiliary impairment or poor nutritional state, the elderly, and patients with cancer.

Prothrombin time should be monitored and exogenous vitamin K administered as indicated.

PRECAUTIONS

General

Prescribing CEFOTAN® in the absence of proven or strongly suspected bacterial infection or a prophylactic indication is unlikely to provide benefit to the patient and increases the risk of the development of drug-resistant bacteria.

As with other broad-spectrum antibiotics, prolonged use of CEFOTAN® may result in overgrowth of nonsusceptible organisms. Careful observation of the patient is essential. If superinfection does occur during therapy, appropriate measures should be taken.

CEFOTAN® should be used with caution in individuals with a history of gastrointestinal disease, particularly colitis.

Information for Patients

Diarrhea is a common problem caused by antibiotics which usually ends when the antibiotic is discontinued. Sometimes after starting treatment with antibiotics, patients can develop watery and bloody stools (with or without stomach cramps and fever) even as late as two or more months after having taken the last dose of the antibiotic. If this occurs, patients should contact their physician as soon as possible.

Patients should be counseled that antibacterial drugs, including CEFOTAN®, should only be used to treat bacterial infections. They do not treat viral infections (e.g., the common cold). When CEFOTAN® is prescribed to treat a bacterial infection, patients should be told that although it is common to feel better early in the course of therapy, the medication should be taken exactly as directed. Skipping doses or not completing the full course of therapy may (1) decrease the effectiveness of the immediate treatment and (2) increase the likelihood that bacteria will develop resistance and will not be treatable by CEFOTAN® (Cefotetan for Injection, USP) or other antibacterial drugs in the future.

As with some other cephalosporins, a disulfiram-like reaction characterized by flushing, sweating, headache, and tachycardia may occur when alcohol (beer, wine, etc.) is ingested within 72 hours after CEFOTAN® (Cefotetan for Injection, USP) administration. Patients should be cautioned about the ingestion of alcoholic beverages following the administration of CEFOTAN®.

Drug Interactions

Increases in serum creatinine have occurred when CEFOTAN® was given alone. If CEFOTAN® and an aminoglycoside are used concomitantly, renal function should be carefully monitored, because nephrotoxicity may be potentiated.

Drug/Laboratory Test Interactions

The administration of CEFOTAN® may result in a false positive reaction for glucose in the urine using Clinitest®‡, Benedict’s solution, or Fehling’s solution. It is recommended that glucose tests based on enzymatic glucose oxidase be used.

As with other cephalosporins, high concentrations of cefotetan may interfere with measurement of serum and urine creatinine levels by Jaffé reaction and produce false increases in the levels of creatinine reported.

Carcinogenesis, Mutagenesis, Impairment of Fertility

Although long-term studies in animals have not been performed to evaluate carcinogenic potential, no mutagenic potential of cefotetan was found in standard laboratory tests.

Cefotetan has adverse effects on the testes of prepubertal rats. Subcutaneous administration of 500 mg/kg/day (approximately 0.8 times the maximum adult human dose on a body surface area basis) on days 6 to 35 of life (thought to be developmentally analogous to late childhood and prepuberty in humans) resulted in reduced testicular weight and seminiferous tubule degeneration in 10 of 10 animals. Affected cells included spermatogonia and spermatocytes; Sertoli and Leydig cells were unaffected. Incidence and severity of lesions were dose-dependent; at 120 mg/kg/day (0.2 times the maximum human dose on a body surface area basis) only 1 of 10 treated animals was affected, and the degree of degeneration was mild.

Similar lesions have been observed in experiments of comparable design with other methylthiotetrazole-containing antibiotics and impaired fertility has been reported, particularly at high dose levels. No testicular effects were observed in 7-week-old rats treated with up to 1000 mg/kg/day subcutaneous for 5 weeks, or in infant dogs (3 weeks old) that received up to 300 mg/kg/day intravenous for 5 weeks (both 1.6 times the maximum recommended human dose on a body surface area basis). The relevance of these findings to humans is unknown.

Pregnancy

Teratogenic Effects.

There are, however, no adequate and well-controlled studies in pregnant women. Because animal reproduction studies are not always predictive of human response, this drug should be used during pregnancy only if clearly needed.

Reproduction studies have been performed in rats and monkeys at doses up to 2000 and 600 mg/kg/day (3 and 2 times the maximum recommended human dose on a body surface area basis, respectively), and have revealed no evidence of impaired fertility or harm to the fetus due to cefotetan.

Nursing Mothers

Cefotetan is excreted in human milk in very low concentrations. Caution should be exercised when cefotetan is administered to a nursing woman.

Pediatric Use

Safety and effectiveness in pediatric patients have not been established.

Geriatric Use

Of the 925 subjects who received cefotetan in clinical studies, 492 (53%) were 60 years and older, while 76 (8%) were 80 years and older. No overall differences in safety or effectiveness were observed between these subjects and younger subjects, and the other reported clinical experience has not identified differences in responses between elderly and younger patients, but greater sensitivity of some older individuals cannot be ruled out.

This drug is known to be substantially excreted by the kidney, and the risk of toxic reactions to this drug may be greater in patients with impaired renal function. Because elderly patients are more likely to have decreased renal function, care should be taken in dose selection, and it may be useful to monitor renal function (see DOSAGE AND ADMINISTRATION, Impaired Renal Function).

ADVERSE REACTIONS

In clinical studies, the following adverse effects were considered related to CEFOTAN therapy. Those appearing in italics have been reported during postmarketing experience.

Gastrointestinal: symptoms occurred in 1.5% of patients, the most frequent were diarrhea (1 in 80) and nausea (1 in 700); pseudomembranous colitis. Onset of pseudomembranous colitis symptoms may occur during or after antibiotic treatment or surgical prophylaxis (see WARNINGS).

Hematologic: laboratory abnormalities occurred in 1.4% of patients and included eosinophilia (1 in 200), positive direct Coombs test (1 in 250), and thrombocytosis (1 in 300); agranulocytosis, hemolytic anemia, leukopenia, thrombocytopenia, and prolonged prothrombin time with or without bleeding.

Hepatic: enzyme elevations occurred in 1.2% of patients and included a rise in ALT (SGPT) (1 in 150), AST (SGOT) (1 in 300), alkaline phosphatase (1 in 700), and LDH (1 in 700).

Hypersensitivity: reactions were reported in 1.2% of patients and included rash (1 in 150) and itching (1 in 700); anaphylactic reactions and urticaria.

Local: effects were reported in less than 1% of patients and included phlebitis at the site of injection (1 in 300), and discomfort (1 in 500).

Renal: Elevations in BUN and serum creatinine have been reported.

Urogenital: Nephrotoxicity has rarely been reported.

Miscellaneous: Fever

In addition to the adverse reactions listed above which have been observed in patients treated with cefotetan, the following adverse reactions and altered laboratory tests have been reported for cephalosporin-class antibiotics: pruritus, Stevens-Johnson syndrome, erythema multiforme, toxic epidermal necrolysis, vomiting, abdominal pain, colitis, superinfection, vaginitis including vaginal candidiasis, renal dysfunction, toxic nephropathy, hepatic dysfunction including cholestasis, aplastic anemia, hemorrhage, elevated bilirubin, pancytopenia, and neutropenia.

Several cephalosporins have been implicated in triggering seizures, particularly in patients with renal impairment, when the dosage was not reduced (see DOSAGE AND ADMINISTRATION and OVERDOSAGE). If seizures associated with drug therapy occur, the drug should be discontinued. Anticonvulsant therapy can be given if clinically indicated.

To report SUSPECTED ADVERSE REACTIONS, contact PAI Pharma at 1-800-845-8210, or FDA at 1-800-FDA-1088 or www.fda.gov/medwatch.

OVERDOSAGE

Information on overdosage with CEFOTAN® in humans is not available. If overdosage should occur, it should be treated symptomatically and hemodialysis considered, particularly if renal function is compromised.

DOSAGE AND ADMINISTRATION

Treatment

The usual adult dosage is 1 gram (g) or 2 grams of CEFOTAN® (Cefotetan for Injection, USP) administered intravenously or intramuscularly. Proper dosage and route of administration should be determined by the condition of the patient, severity of the infection, and susceptibility of the causative organism.

General Guidelines for Dosage of CEFOTAN® (Cefotetan for Injection, USP)
Type of Infection | Daily Dose | Frequency and Route
Urinary Tract | 1 g to 4 g | 500 mg every 12 hours intravenous or intramuscular; 1 or 2 g every 24 hours intravenous or intramuscular; 1 or 2 g every 12 hours intravenous or intramuscular
Skin & Skin Structure
Mild - Moderatea | 2 g | 2 g every 24 hours intravenous; 1 g every 12 hours intravenous or intramuscular
Severe | 4 g | 2 g every 12 hours intravenous
Other Sites | 2 g to 4 g | 1 g or 2 g every 12 hours intravenous or intramuscular
Severe | 4 g | 2 g every 12 hours intravenous
Life-Threatening | 6 gb | 3 g every 12 hours intravenous

General Guidelines for Dosage of CEFOTAN® (Cefotetan for Injection, USP)
Type of Infection | Daily Dose | Frequency and Route
Urinary Tract | 1 to 4 grams | 500 mg every 12 hours IV or IM; 1 or 2 g every 24 hours IV or IM; 1 or 2 g every 12 hours IV or IM
Urinary Tract |  | 500 mg every 12 hours IV or IM; 1 or 2 g every 24 hours IV or IM; 1 or 2 g every 12 hours IV or IM
Skin & Skin Structure; Mild - Moderatea; Severe
Skin & Skin Structure; Mild - Moderatea; Severe | 2 grams | 2 g every 24 hours IV; 1 g every 12 hours IV or IM
Skin & Skin Structure; Mild - Moderatea; Severe | 4 grams | 2 g every 12 hours IV
Other Sites | 2 to 4 grams | 1 or 2 g every 12 hours IV or IM
Severe | 4 grams | 2 g every 12 hours IV
Life-Threatening | 6 gramsb | 3 g every 12 hours IV

a Klebsiella pneumoniae skin and skin structure infections should be treated with 1 or 2 grams every 12 hours IV or IM.

b Maximum daily dosage should not exceed 6 grams.

If Chlamydia trachomatis is a suspected pathogen in gynecologic infections, appropriate antichlamydial coverage should be added, since cefotetan has no activity against this organism.

Prophylaxis

To prevent postoperative infection in clean contaminated or potentially contaminated surgery in adults, the recommended dosage is 1 or 2 g of CEFOTAN® (Cefotetan for Injection, USP) administered once, intravenously, 30 to 60 minutes prior to surgery. In patients undergoing cesarean section, the dose should be administered as soon as the umbilical cord is clamped.

Impaired Renal Function

When renal function is impaired, a reduced dosage schedule must be employed. The following dosage guidelines may be used.

DOSAGE GUIDELINES FOR PATIENTS WITH IMPAIRED RENAL FUNCTION
Creatinine Clearance; mL/min | Dose | Frequency
Greater than 30 | Usual Recommended Dosage* | Every 12 hours
10 to 30 | Usual Recommended Dosage* | Every 24 hours
Less than 10 | Usual Recommended Dosage* | Every 48 hours

* Dose determined by the type and severity of infection, and susceptibility of the causative organism.

Alternatively, the dosing interval may remain constant at 12 hour intervals, but the dose reduced to one-half the usual recommended dose for patients with a creatinine clearance of 10 to 30 mL/min, and one-quarter the usual recommended dose for patients with a creatinine clearance of less than 10 mL/min.

When only serum creatinine levels are available, creatinine clearance may be calculated from the following formula. The serum creatinine level should represent a steady state of renal function.

Males: Weight (kg) x (140 - age)

72 x serum creatinine (mg/100 mL)

Females: 0.85 x value for males

Cefotetan is dialyzable and it is recommended that for patients undergoing intermittent hemodialysis, one-quarter of the usual recommended dose be given every 24 hours on days between dialysis and one-half the usual recommended dose on the day of dialysis.

Preparation of Solution

For Intravenous Use

Reconstitute with Sterile Water for Injection. Shake to dissolve and let stand until clear.

Vial Size | Amount of; Diluent; Added (mL) | Approximate Withdrawable; Vol (mL) | Approximate; Average Concentration (mg/mL)
1 gram | 10 | 10.5 | 95
2 gram | 10 to 20 | 11 to 21 | 182 to 95

For Intramuscular Use

Reconstitute with Sterile Water for Injection; Bacteriostatic Water for Injection; Sodium Chloride Injection 0.9%, USP; 0.5% Lidocaine HCl; or 1% Lidocaine HCl. Shake to dissolve and let stand until clear.

Vial Size | Amount of; Diluent; Added (mL) | Approximate Withdrawable; Vol (mL) | Approximate; Average Concentration; (mg/mL)
1 gram | 2 | 2.5 | 400
2 gram | 3 | 4 | 500

Intravenous Administration

The intravenous route is preferable for patients with bacteremia, bacterial septicemia, or other severe or life-threatening infections, or for patients who may be poor risks because of lowered resistance resulting from such debilitating conditions as malnutrition, trauma, surgery, diabetes, heart failure, or malignancy, particularly if shock is present or impending.

For intermittent intravenous administration, a solution containing 1 gram or 2 grams of CEFOTAN® (Cefotetan for Injection, USP) in Sterile Water for Injection can be injected over a period of three to five minutes. Using an infusion system, the solution may also be given over a longer period of time through the tubing system by which the patient may be receiving other intravenous solutions. Butterfly® or scalp vein-type needles are preferred for this type of infusion. However, during infusion of the solution containing CEFOTAN® (Cefotetan for Injection, USP), it is advisable to discontinue temporarily the administration of other solutions at the same site.

NOTE: Solutions of cefotetan must not be admixed with solutions containing aminoglycosides. If CEFOTAN® and aminoglycosides are to be administered to the same patient, they must be administered separately and not as a mixed injection.

Intramuscular Administration

As with all intramuscular preparations, CEFOTAN® (Cefotetan for Injection, USP) should be injected well within the body of a relatively large muscle such as the upper outer quadrant of the buttock (i.e., gluteus maximus); aspiration is necessary to avoid inadvertent injection into a blood vessel.

Compatibility and Stability

Frozen samples should be thawed at room temperature before use. After the periods mentioned below, any unused solutions or frozen material should be discarded. DO NOT REFREEZE.

NOTE: Solutions of CEFOTAN® (Cefotetan for Injection, USP) must not be admixed with solutions containing aminoglycosides. If CEFOTAN® (Cefotetan for Injection, USP) and aminoglycosides are to be administered to the same patient, they must be administered separately and not as a mixed injection. DO NOT ADD SUPPLEMENTARY MEDICATION.

CEFOTAN® (Cefotetan for Injection, USP) reconstituted as described above (see DOSAGE AND ADMINISTRATION, Preparation of Solution) maintains satisfactory potency for 24 hours at room temperature (25°C/77°F), for 96 hours under refrigeration (5°C/41°F), and for at least 1 week in the frozen state (-20°C/-4°F). After reconstitution and subsequent storage in disposable glass or plastic syringes, CEFOTAN® (Cefotetan for Injection, USP) is stable for 24 hours at room temperature and 96 hours under refrigeration.

NOTE: Parenteral drug products should be inspected visually for particulate matter and discoloration prior to administration whenever solution and container permit.

HOW SUPPLIED

CEFOTAN® (Cefotetan for Injection, USP) is a dry, white to pale yellow powder supplied in vials containing cefotetan disodium equivalent to 1 g and 2 g cefotetan activity for intravenous and intramuscular administration. The vials should be stored at 20°C to 25° C (68° to 77° F) [see USP Controlled Room Temperature] and should be protected from light.

The following packages are available:

NDC No. | Strength | Supplied
0121-0976-10 | 1 gram | 10 mL vial, packaged in a tray of 10
0121-0977-10 | 2 grams | 20 mL vial, packaged in a tray of 10

Vial stoppers do not contain natural rubber latex.

‡Clinitest® is a registered trademark of Siemens Healthcare Diagnostics Inc.

CEFOTAN® is a registered trademark of PAI Holdings, LLC.

Distributed by:

PAI Pharma

Greenville, SC 29605

Made in Italy

I097609770723
Rev 07/2023

PACKAGE LABEL. CARTON PRINCIPAL DISPLAY PANEL

NDC 0121-0976-10

CEFOTAN®
(Cefotetan for Injection, USP)

PAI Pharma

Equivalent to 1 gram Cefotetan per vial

Rx only

10 - 10 mL Vials

Protect from Light
KEEP TOP CLOSED

Each Vial contains:
Cefotetan disodium equivalent to
1 g cefotetan activity. Sodium content is
80 mg (3.5 mEq) per gram of cefotetan.

Must be reconstituted.

For intravenous infusion or intramuscular injection.

PACKAGE LABEL. CARTON PRINCIPAL DISPLAY PANEL

NDC 0121-0977-10

CEFOTAN®
(Cefotetan for Injection, USP)

PAI Pharma

Equivalent to 2 grams Cefotetan per vial

Rx only

10 - 20 mL Vials

Protect from Light
KEEP TOP CLOSED
Must be reconstituted.
For intravenous infusion or intramuscular injection.

Each Vial contains:
Cefotetan disodium equivalent to
2 g cefotetan activity. Sodium content is
80 mg (3.5 mEq) per gram of cefotetan.

PACKAGE LABEL. VIAL PRINCIPAL DISPLAY PANEL

NDC 0121-0976-55

CEFOTAN®
(Cefotetan for Injection, USP)

1 gram per vial*

Must be reconstituted.
For intravenous infusion
or intramuscular injection.

PAI Pharma

Rx only

PACKAGE LABEL. VIAL PRINCIPAL DISPLAY PANEL

NDC 0121-0977-55

CEFOTAN®
(Cefotetan for Injection, USP)

2 gram per vial*

Must be reconstituted.
For intravenous infusion
or intramuscular injection.

PAI Pharma

Rx only